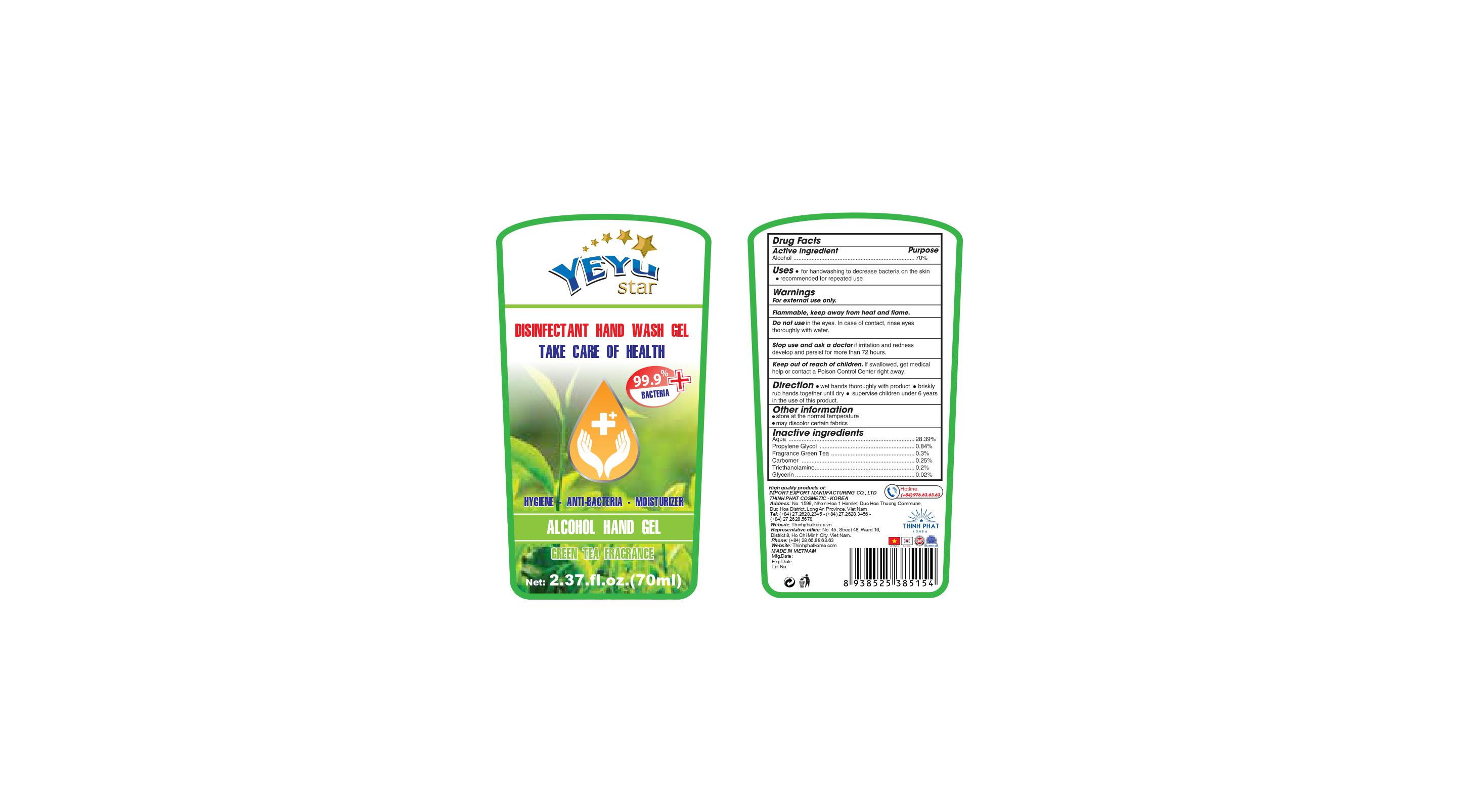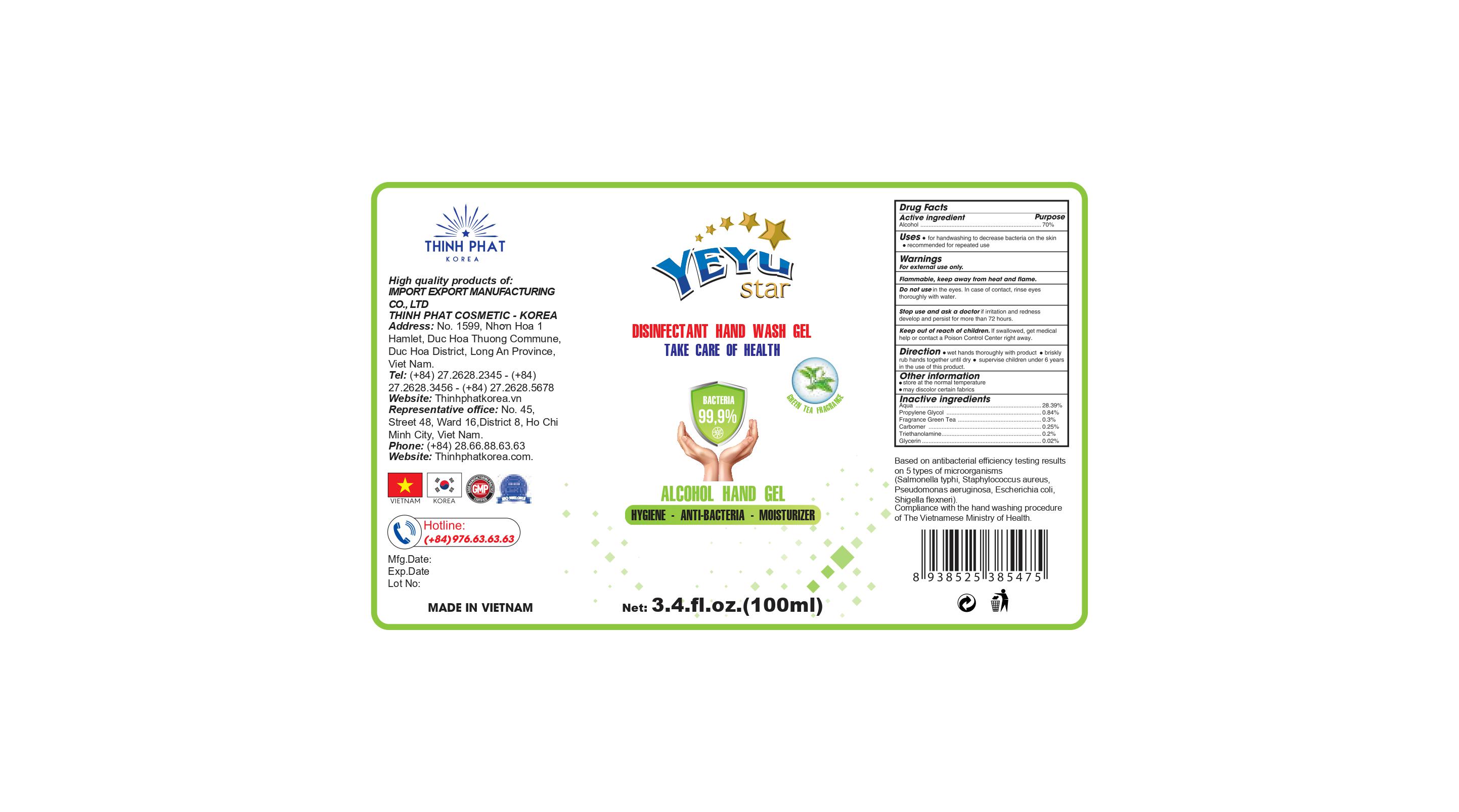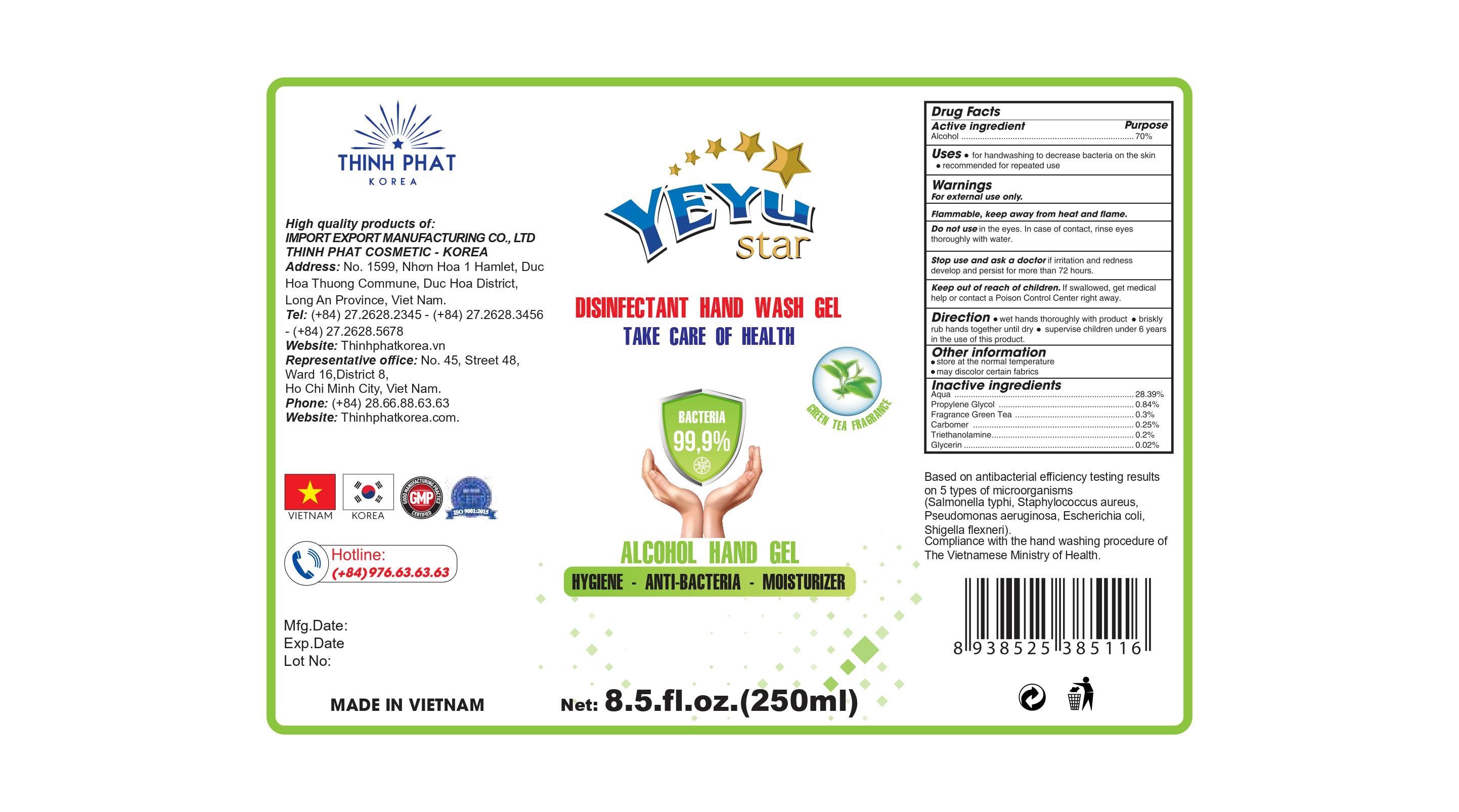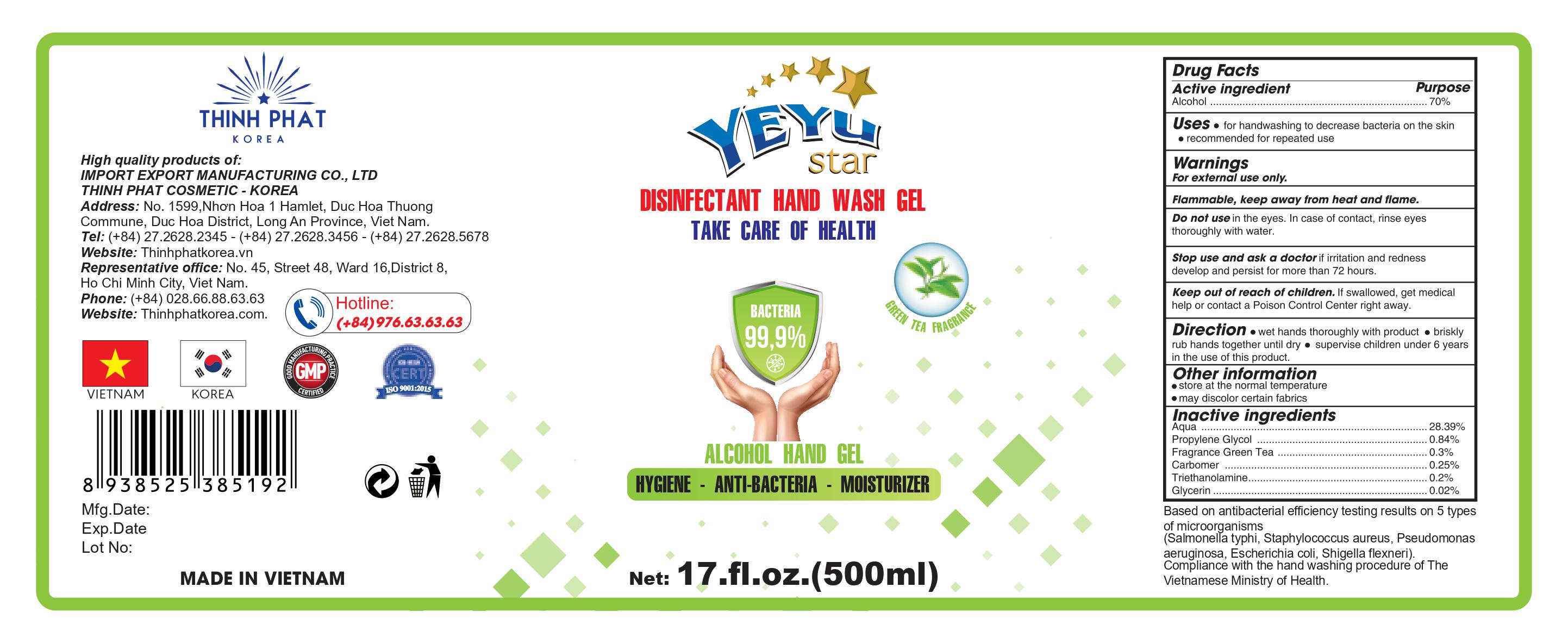 DRUG LABEL: Hand Sanitizer
NDC: 78819-101 | Form: GEL
Manufacturer: THINH PHAT - KOREA SX TM XNK PHARMACEUTICAL COSMETICS COMPANY
Category: otc | Type: HUMAN OTC DRUG LABEL
Date: 20201015

ACTIVE INGREDIENTS: ALCOHOL 70 mL/100 mL
INACTIVE INGREDIENTS: GLYCERIN 0.02 mL/100 mL; CARBOMER 940 0.25 mL/100 mL; WATER 28.39 mL/100 mL; PROPYLENE GLYCOL 0.84 mL/100 mL; TROLAMINE 0.2 mL/100 mL; GREEN TEA LEAF 0.3 mL/100 mL

This is a hand sanitizer manufactured according to the Temporary Policy for Preparation of Certain Alcohol-Based Hand Sanitizer Products During the Public Health Emergency (CoViD-19); Guidance for Industry.

The hand sanitizer is manufactured using only the following United States Pharmacopoeia (USP) grade ingredients in the preparation of the product (percentage in final product formulation) consistent with World Health Organization (WHO) recommendations:

1. Alcohol (ethanol) (USP or Food Chemical Codex (FCC) grade) (80%, volume/volume (v/v)) in an aqueous solution denatured according to Alcohol and Tobacco Tax and Trade Bureau regulations in 27 CFR part 20.
2. Glycerol (1.45% v/v).
3. Hydrogen peroxide (0.125% v/v).
4. Sterile distilled water or boiled cold water.

The firm does not add other active or inactive ingredients. Different or additional ingredients may impact the quality and potency of the product.

Active Ingredient(s)

Alcohol 70% v/v. Purpose: Antiseptic

Purpose

Antiseptic, Hand Sanitizer

Use

for hand washing to decrease bacteria on the skin.

recommended for repeated use.

Warnings

For external use only. Flammable. Keep away from heat or flame

Do not use

- in the eyes
- in case of contact, rinse eyes thoroughly with water

When using this product keep out of eyes, ears, and mouth. In case of contact with eyes, rinse eyes thoroughly with water.
Stop use and ask a doctor if irritation or rash occurs. These may be signs of a serious condition.
Keep out of reach of children. If swallowed, get medical help or contact a Poison Control Center right away.

Stop use and ask a doctor if irritation or rash occurs. These may be signs of a serious condition.

Keep out of reach of children. If swallowed, get medical help or contact a Poison Control Center right away.

Directions

- wet hands thoroughly with product
- brisky rub hands together until dry
- Supervise children under 6 years in the use of this product.

Other information

- Store between 15-30C (59-86F)
- Avoid freezing and excessive heat above 40C (104F)

Inactive ingredients

auqa, propylene glycol, fragrance green tea, carbomer, triethanolamine, glycerin

RECENT MAJOR CHANGES

Use: Rewording

Directions: rewording

Package Label - Principal Display Panel

70 mL NDC: 78819-101-01

100 mL NDC: 78819-101-02

250 mL NDC: 78819-101-03

500 mL NDC: 78819-101-04